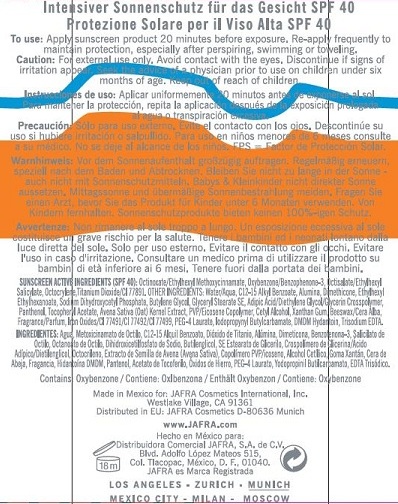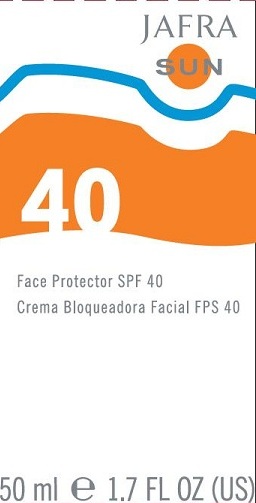 DRUG LABEL: FACE PROTECTOR
NDC: 68828-054 | Form: LOTION
Manufacturer: JAFRA COSMETICS INTERNATIONAL
Category: otc | Type: HUMAN OTC DRUG LABEL
Date: 20120514

ACTIVE INGREDIENTS: OCTINOXATE 7.5 g/100 mL; OXYBENZONE 2 g/100 mL; OCTISALATE 5 g/100 mL; OCTOCRYLENE 2 g/100 mL; TITANIUM DIOXIDE 2 g/100 mL
INACTIVE INGREDIENTS: WATER; ALKYL (C12-15) BENZOATE; ALUMINUM OXIDE; DIMETHICONE; ETHYLHEXYL ETHYLHEXANOATE; SODIUM PHOSPHATE, MONOBASIC; BUTYLENE GLYCOL; GLYCERYL STEARATE SE; DIETHYLENE GLYCOL ADIPATE; OAT; POVIDONE K30; CETYL ALCOHOL; YELLOW WAX; FERRIC OXIDE RED; FERRIC OXIDE YELLOW; FERROSOFERRIC OXIDE; PEG-4 LAURATE; DMDM HYDANTOIN; IODOPROPYNYL BUTYLCARBAMATE; PANTHENOL; .ALPHA.-TOCOPHEROL ACETATE; XANTHAN GUM; EDETATE TRISODIUM

FACE PROTECTOR SPF 40

SUNSCREEN ACTIVE INGREDIENT (SPF 40):
OCTINOXATE/ETHYLHEXYL METHOXYCINNAMATE, OXYBENZONE/BENZOPHENONE-3, OCTISALATE/ETHYLHEXYL SALICYLATE, OCTOCRYLENE, TITANIUM DIOXIDE/CI 77891.

PURPOSE: SUNSCREEN

INACTIVE INGREDIENT

OTHER INGREDIENTS: WATER/AQUA, C12-15 ALKYL BENZOATE, ALUMINA, DIMETHICONE, ETHYLHEXYL ETHYLHEXANOATE, SODIUM DIHYDROXYCETYL PHOSPHATE, BUTYLENE GLYCOL, GLYCERYL STEARATE SE, ADIPIC ACID/DIETHYLENE GLYCOL/GLYCERIN CROSSPOLYMER, PANTHENOL, TOCOPHERYL ACETATE, AVENA SATIVA (OAT) KERNEL EXTRACT, PVP/EICOSENE COPOLYMER, CETYL ALCOHOL, XANTHAN GUM, BEESWAX/CERA ALBA, FRAGRANCE/PARFUM, IRON OXIDES/CI 77491/CI 77492/CI 77499, PEG-4 LAURATE, IODOPROPYNYL BUTYLCARBAMATE, DMDM HYDANTOIN, TRISODIUM EDTA.

INDICATIONS AND USAGE

FACE PROTECTOR SPF 40

DOSAGE AND ADMINISTRATION

TO USE: APPLY SUNSCREEN PRODUCT 20 MINUTES BEFORE EXPOSURE. RE-APPLY FREQUENTLY TO MAINTAIN PROTECTION, ESPECIALLY AFTER PERSPIRING, SWIMMING OR TOWELING.

DISCONTINUE USE IF IRRITATION OCCURS.

KEEP OUT OF REACH OF CHILDREN.

PACKAGE LABEL

JAFRA SUN

FACE PROTECTOR SPF 40

WARNINGS

CAUTION: FOR EXTERNAL USE ONLY. AVOID CONTACT WITH EYES.